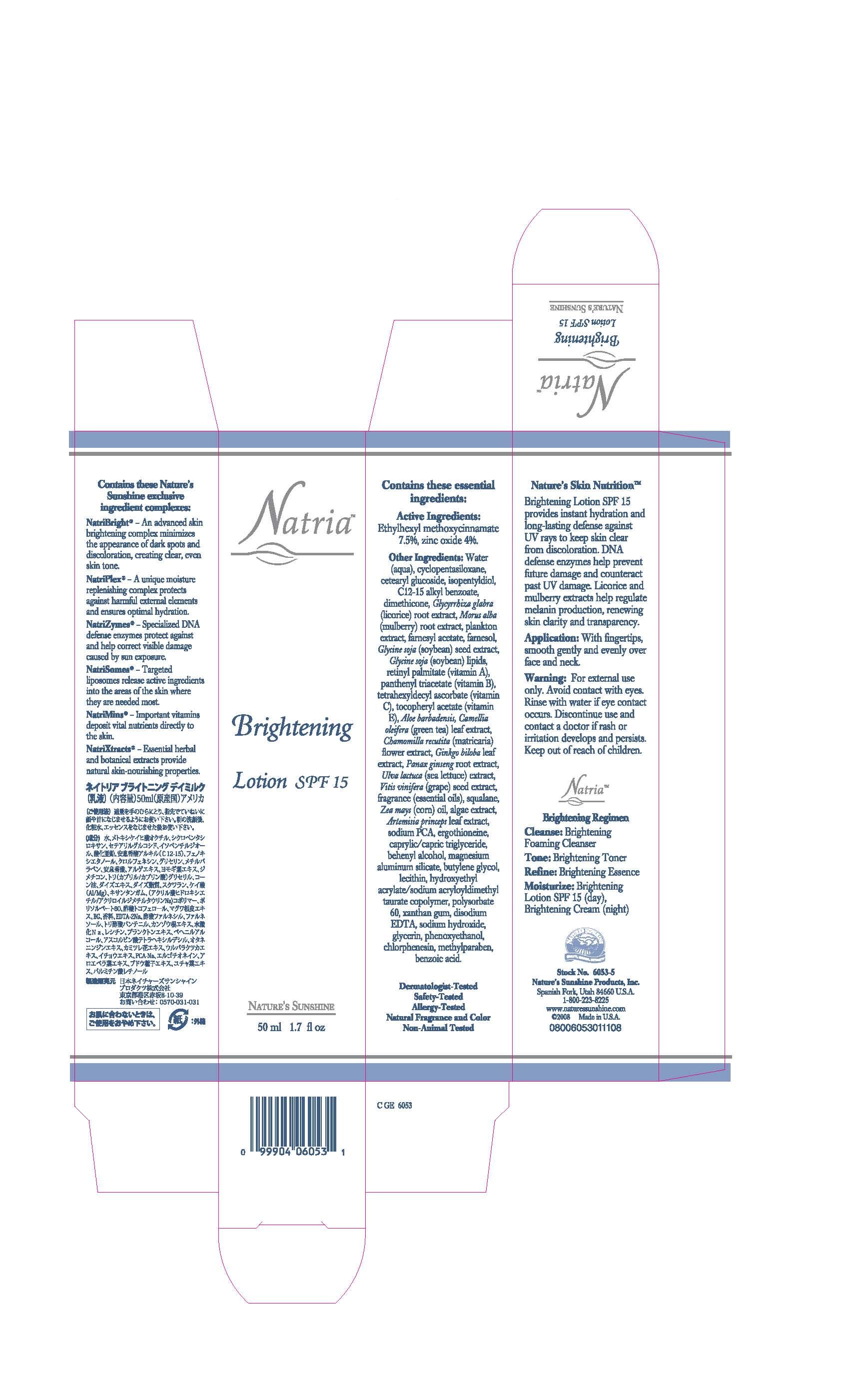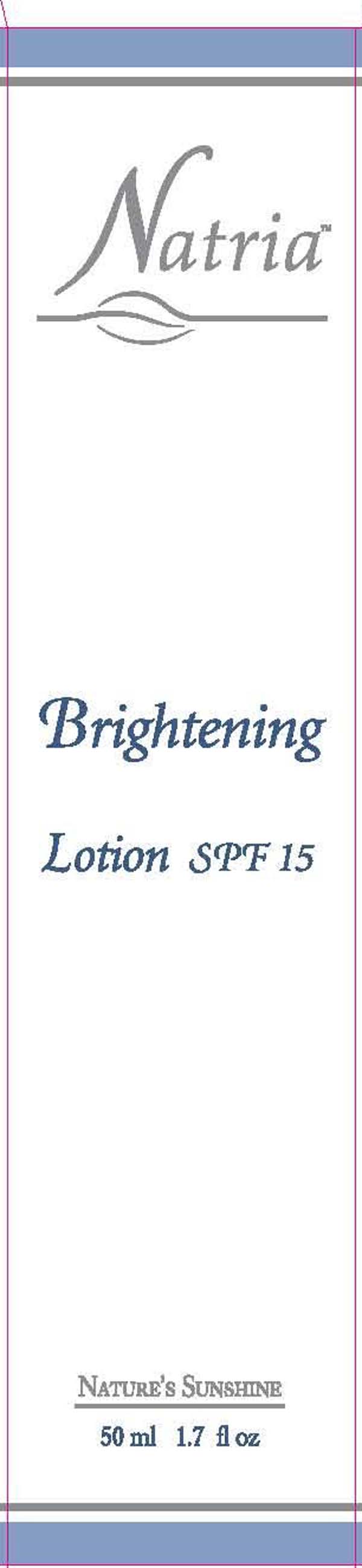 DRUG LABEL: Natria
NDC: 44717-538 | Form: CREAM
Manufacturer: Wasatch Product Development
Category: otc | Type: HUMAN OTC DRUG LABEL
Date: 20110311

ACTIVE INGREDIENTS: OCTINOXATE 7.5 mL/100 mL; ZINC OXIDE 2.5 mL/100 mL
INACTIVE INGREDIENTS: CYCLOMETHICONE 5; CETEARYL GLUCOSIDE; ISOPENTYLDIOL; ALKYL (C12-15) BENZOATE; DIMETHICONE; GLYCYRRHIZA GLABRA; TETRAHEXYLDECYL ASCORBATE; SQUALENE; SODIUM PYRROLIDONE CARBOXYLATE

Natria Brightening Lotion SPF 15

Active Ingredients
Ethylhexyl Methoxycinnamate 7.5%
Zinc Oxide 4%

PURPOSE

provides instant hydration and long- lasting defense against UV rays to keep skin clear from discoloration

Keep out of reach of children.

INDICATIONS AND USAGE

For external use only.

WARNINGS

Avoid contact with eyes. Rinse with water if eye contact occurs. Discontinue use and contact a doctor if rash or irritation develops and persists.

DOSAGE AND ADMINISTRATION

with fingertips, smooth gently and evenly over face and neck .

INACTIVE INGREDIENT

Ingredients: Water (Aqua), Cyclopentasiloxane, Cetearyl Glucoside, Isopentyldiol, C12-15 Alkyl Benzoate, Dimethicone, Glycyrrhiza Glabra (Licorice) Root Extract, Morus Alba (Mulberry) Root Extract, Plankton Extract, Farnesyl Acetate, Farnesol, Glycine Soja (Soybean) Lipids, Retinyl Palmitate (Vitamin A), Panthenyl Triacetate (Vitamin B), Tetrahexyldecyl Ascorbate (Vitamin C), Tocopheryl Acetate (Vitamin E), Aloe Barbadensis, Camellia Oleifera (Green Tea) Leaf Extract, Chamomilla Recutita (Matricaria) Flower Extract, Ginkgo Biloba Leaf Extract, Panax Ginseng Root Extract, Ulva Lactuca (Sea Lettuce) Extract, Vitis Vinifera (Grape) Seed Extract, Fragrance (Essential Oils), Squalane, Zea Mays (Corn) Oil, Algae Extract, Artemisia Princeps Leaf Extract, Sodium PCA, Ergothioneine, Caprylic/Capric Triglyceride, Behenyl Alcohol, Magnesium Aluminu Silicate, Butylene Glycol, Lecithin, Hydroxyethyl Acrylate/Sodium Acryloyldimethyl Taurate Copolymer, Polysorbate 60, Xanthan Gum, Disodium EDTA, Sodium Hydroxide, Glycerin, Phenoxyethanol, Chlorphenesin, Methylparaben, Benzoic Acid.

PACKAGE LABEL

Natria
Brightening Lotion SPF 15
Nature's Sunshine
50 ml 1.7 fl oz